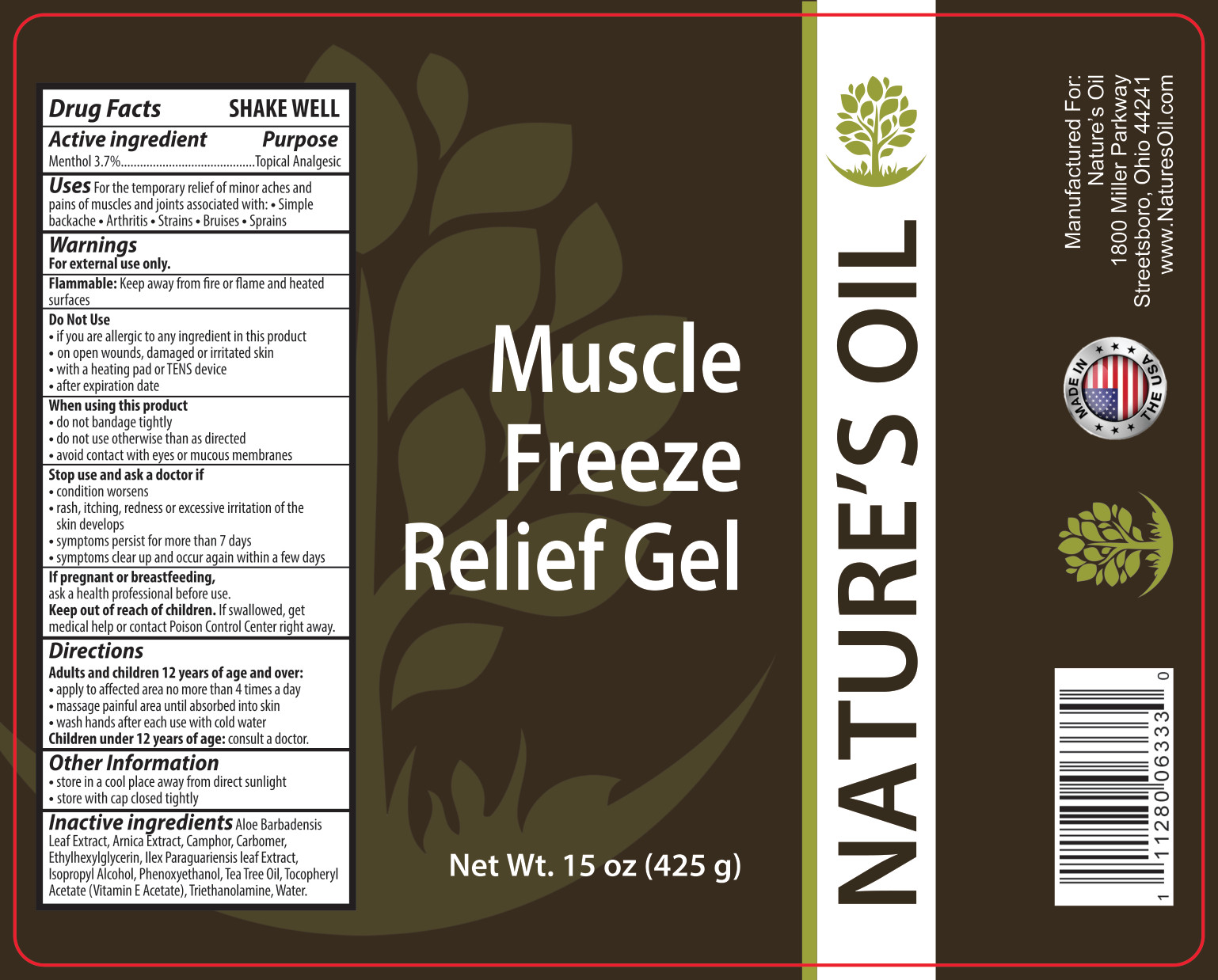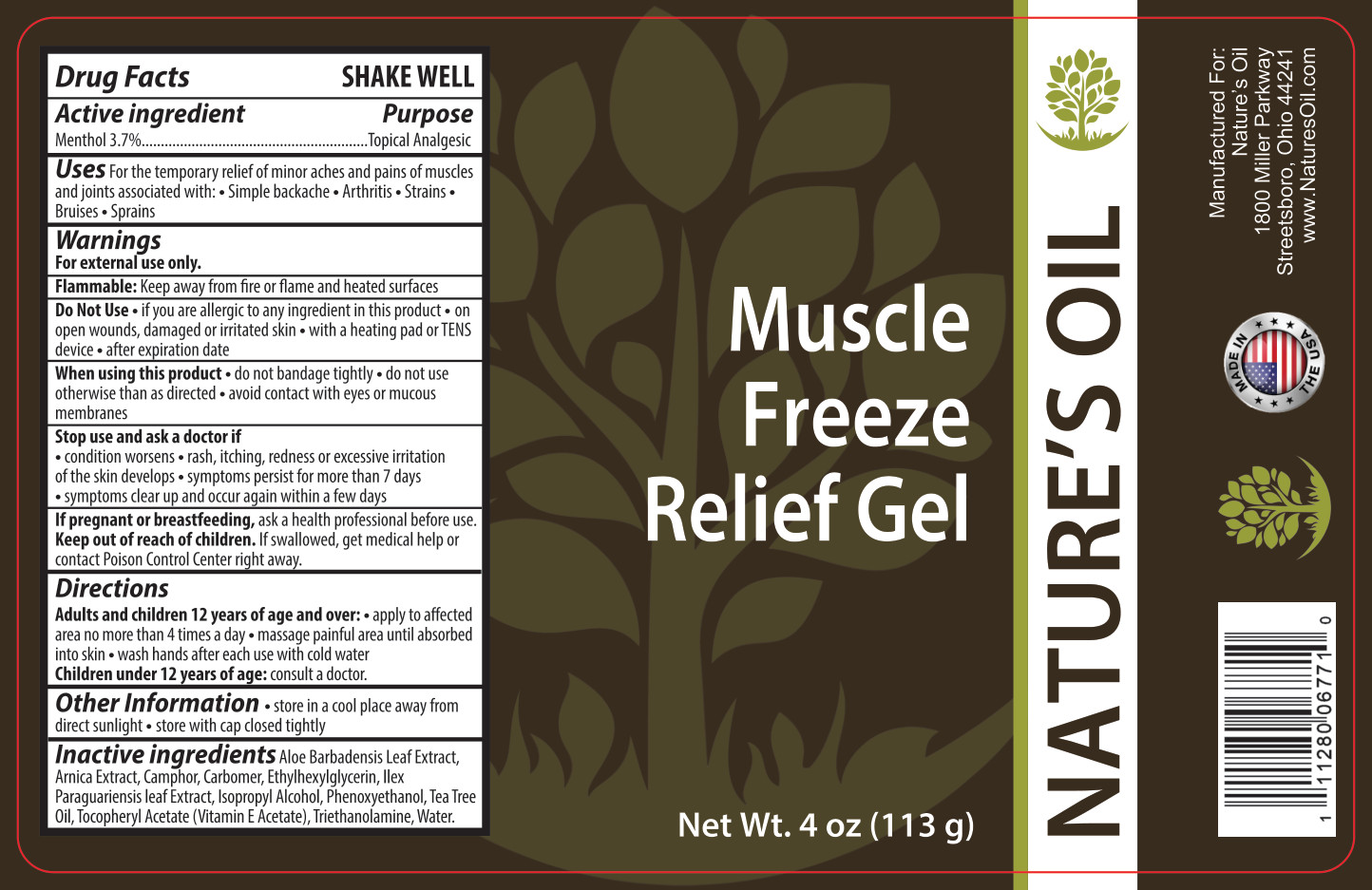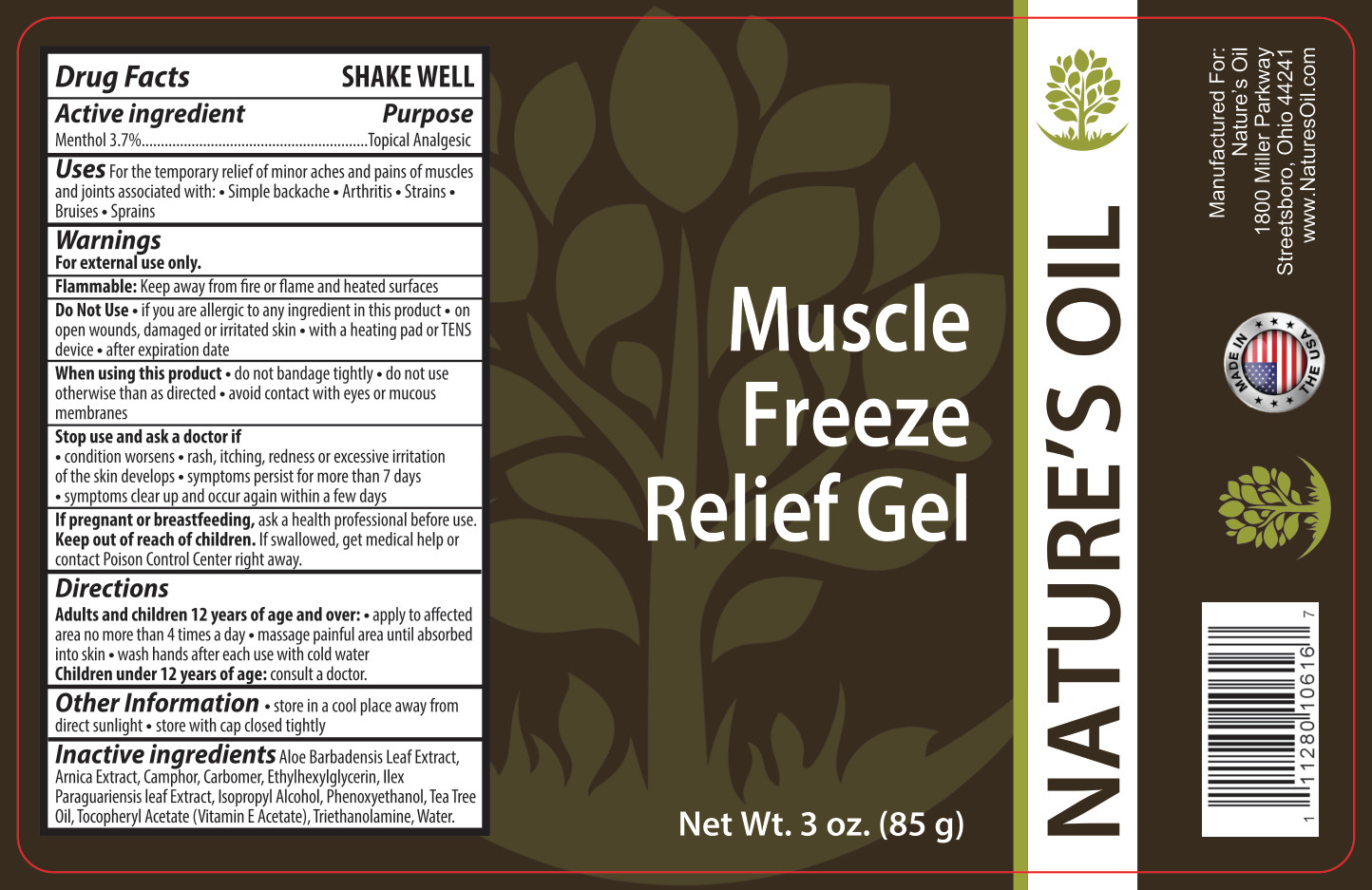 DRUG LABEL: Muscle Freeze Relief
NDC: 66902-410 | Form: GEL
Manufacturer: NATURAL ESSENTIALS, INC.
Category: otc | Type: HUMAN OTC DRUG LABEL
Date: 20241009

ACTIVE INGREDIENTS: MENTHOL, UNSPECIFIED FORM 37 mg/1 g
INACTIVE INGREDIENTS: ALOE VERA LEAF; CARBOMER HOMOPOLYMER TYPE C (ALLYL PENTAERYTHRITOL CROSSLINKED); CAMPHOR (SYNTHETIC); .ALPHA.-TOCOPHEROL ACETATE; ETHYLHEXYLGLYCERIN; ISOPROPYL ALCOHOL; PHENOXYETHANOL; ILEX PARAGUARIENSIS LEAF; TROLAMINE; WATER

Drug Facts

SHAKE WELL

Active ingredient

Menthol 3.7%

Purpose

Topical Analgesic

Uses

For the temporary relief of minor aches and pains of muscles and joints associated with:

- Simple backache
- Arthritis
- Strains
- Bruises
- Sprains

Warnings

For external use only.

Flammable:Keep away from fire or flame and heated surfaces

Do Not Use

- if you are allergic to any ingredient in this product
- on open wounds, damaged or irritated skin
- with a heating pad or TENS device
- after expiration date

When using this product

- do not bandage tightly
- do not use otherwise than as directed
- avoid contact with eyes or mucous membranes

Stop use and ask a doctor if

- condition worsens
- rash, itching, redness or excessive irritation of the skin develops
- symptoms persist for more than 7 days
- symptoms dear up and occur again within a few days

PREGNANCY OR BREAST FEEDING

If pregnant or breastfeeding,ask a health professional before use.

Keep out of reach of children.If swallowed, get medical help or contact Poison Control Center right away.

Directions

Adults and children 12 years of age and over:

- apply to affected area no more than 4 times a day
- massage painful area until absorbed into skin
- wash hands after each use with cold water

Children under 12 years of age:consult a doctor.

Other Information

- store in a cool place away from direct sunlight
- store with cap closed tightly

Inactive ingredients

Aloe Barbadensis Leaf Extract, Arnica Extract, Camphor, Carbomer, Ethylhexylglycerin, Ilex Paraguariensis leaf Extract, Isopropyl Alcohol, Phenoxyethanol, Tea Tree Oil, Tocopheryl Acetate (Vitamin E Acetate), Triethanolamine, Water.

Principal Display Panel – 85 g Container Label

Muscle
Freeze
Relief Gel

Net Wt. 3 oz. (85 g)

Principal Display Panel – 425 g Container Label

Muscle
Freeze
Relief Gel

Net Wt. 15 oz. (425 g)

Principal Display Panel - 113 g Container Label

Muscle

Freeze

Relief Gel

Net Wt. 4 oz (113 g)